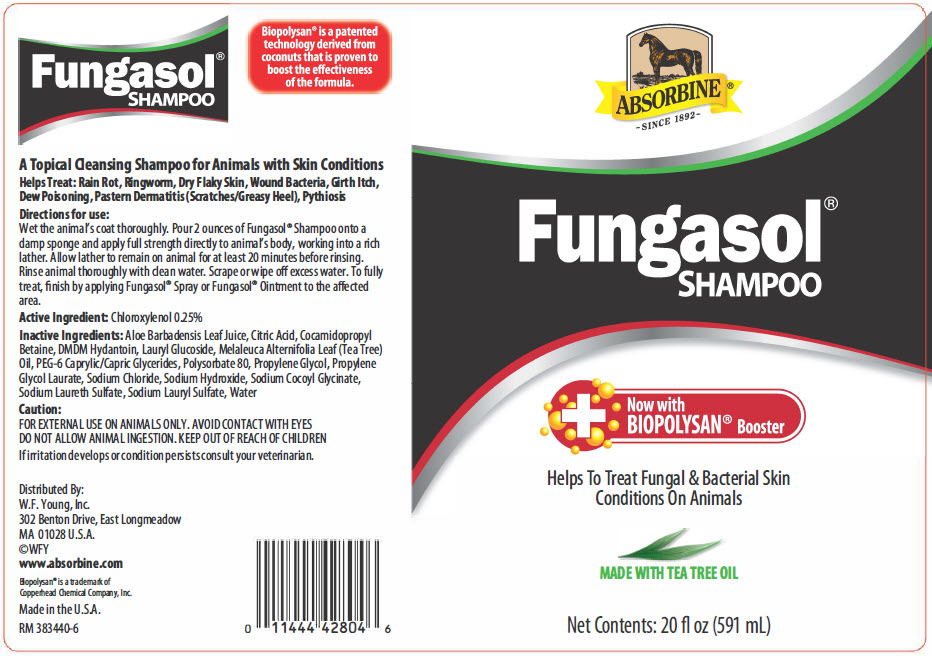 DRUG LABEL: Absorbine Fungasol
NDC: 11444-428 | Form: LIQUID
Manufacturer: W. F. Young, Inc.
Category: animal | Type: OTC ANIMAL DRUG LABEL
Date: 20170428

ACTIVE INGREDIENTS: CHLOROXYLENOL 0.25 g/100 mL

Fungasol®
SHAMPOO

Biopolysan® is a patented technology derived from coconuts that is proven to boost the effectiveness of the formula.

DESCRIPTION

A Topical Cleansing Shampoo for Animals with Skin Conditions

Helps Treat: Rain Rot, Ringworm, Dry Flaky Skin, Wound Bacteria, Girth Itch, Dew Poisoning, Pastern Dermatitis (Scratches/Greasy Heel), Pythiosis

Directions for use:

Wet the animal's coat thoroughly. Pour 2 ounces of Fungasol® Shampoo onto a damp sponge and apply full strength directly to animal's body, working into a rich lather. Allow lather to remain on animal for at least 20 minutes before rinsing. Rinse animal thoroughly with clean water. Scrape or wipe off excess water. To fully treat, finish by applying Fungasol® Spray or Fungasol® Ointment to the affected area.

Active Ingredient: Chloroxylenol 0.25%

INACTIVE INGREDIENT

Inactive Ingredients: Aloe Barbadensis Leaf Juice, Citric Acid, Cocamidopropyl Betaine, DMDM Hydantoin, Lauryl Glucoside, Melaleuca Alternifolia Leaf (Tea Tree) Oil, PEG-6 Caprylic/Capric Glycerides, Polysorbate 80, Propylene Glycol, Propylene Glycol Laurate, Sodium Chloride, Sodium Hydroxide, Sodium Cocoyl Glycinate, Sodium Laureth Sulfate, Sodium Lauryl Sulfate, Water

Caution:

FOR EXTERNAL USE ON ANIMALS ONLY

AVOID CONTACT WITH EYES

DO NOT ALLOW ANIMAL INGESTION

KEEP OUT OF REACH OF CHILDREN

If irritation develops or condition persists consult your veterinarian.

Distributed By:
W.F. Young, Inc.
302 Benton Drive
East Longmeadow, MA
01028 U.S.A.
©WFY

www.absorbine.com

Biopolysan® is a trademark of
Copperhead Chemical Company, Inc.

Made in the U.S.A.

RM 383440

PRINCIPAL DISPLAY PANEL - 591 mL Bottle Label

ABSORBINE®
- SINCE 1892 -

Fungasol®
SHAMPOO

+
Now with
BIOPOLYSAN® Booster

Helps To Treat Fungal & Bacterial Skin
Conditions On Animals

MADE WITH TEA TREE OIL

Net Contents: 20 fl oz (591 mL)